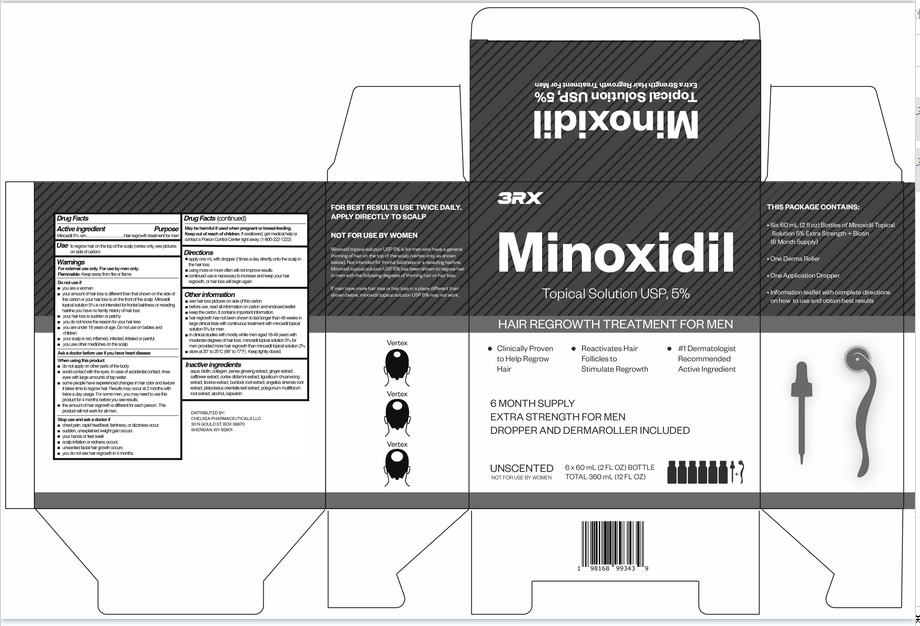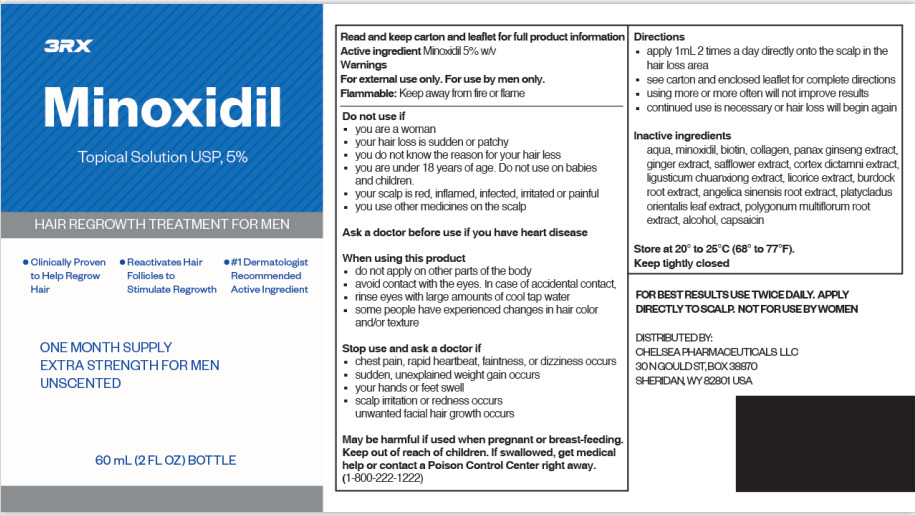 DRUG LABEL: 3RX Minoxidil HAIR REGROWTH TREATMENT FOR MEN
NDC: 84432-001 | Form: LIQUID
Manufacturer: Shenzhen Youbente E-commerce Co., Ltd
Category: otc | Type: HUMAN OTC DRUG LABEL
Date: 20240618

ACTIVE INGREDIENTS: MINOXIDIL 5 g/100 mL
INACTIVE INGREDIENTS: LIGUSTICUM SINENSE SUBSP. CHUANXIONG ROOT; ARCTIUM LAPPA ROOT; FALLOPIA MULTIFLORA ROOT; CAPSAICIN; WATER; BIOTIN; COLLAGEN ALPHA-1(I) CHAIN BOVINE; PANAX JAPONICUS ROOT; GINGER; SAFFLOWER; DICTAMNINE; ANGELICA SINENSIS ROOT; ALCOHOL; LICORICE; PLATYCLADUS ORIENTALIS LEAF

84432-001

Active Ingredient(s)

minoxidil 5%

Purpose

Hair regrowth treatment for men

Use

Use to regrow hair on the top of the scalp (vertex only, see pictures on side of carton)

Warnings

For extermal use only. For use by men only.
Flammable: Keep away from fire or flame

Do not use

■youare a woman
■your amount of hair loss is diferent than that shown on the sideof
this carton or your hair loss is on the front of the scalp. Minoxidil
topical solution 5% is not intended for frontal baldness or receding
hairlineyou have no family history of hair loss
■yourhair loss is suddenor patchy
■youdo not knowthe reason for your hair less
■youareunder 18years of age. Do notuse on babies and
children.
■yourscalp is red, inflamed, infected, itated or painful
■youuse other medicines onthe scalp

WHEN USING

■donot apply on other parts of the body

■avoid contact with the eyes. In case of accidental contact, rinse
eyes with large amounts of tap water.
■some people have experienced changes in hair color and texture
it takes time to regrow hair. Results may occur at 2 months with
twice a day usage. For some men, you may need to use this
product for 4 months before you see results.
■the amount of hair regrowth is different for each person. This
product will not work for all men.

STOP USE

■chest pain, rapid heartbeat, faintness, or dizziness occur
■sudden, unexplained weight gain occurs
■your hands or feet swell
■scalp initation or redness occurs
■unwanted facial hair growthoocurs
■youdo not see hair regrowth in 4 months

Keep out of reach of children. If swallowed, get medical help or
oontact a Poison Control Center right away

Directions

■apply one mLwith dropper 2 times a day direty onto the scalpin the hair loss
■using more or more often will not improve results
■continued use is neoessary to increase and keep your hair
regrowth, or hair loss will begin again

Other information

■see hair loss pictures on side of this carton
■before use, read all information on carton and enclosed lealflet
■keepthe carton. It contains important infomation.
■hair regrowth has not been shown to last longer than 48 weeks in
large dlinical trials with continuous treatment with minoxidil topical solution 5% for men
■indlinical studies with mosty white men aged 18-49 years with moderate degrees of hair loss, minoxidil topical solution 5% for
men provided more hair regrowth than minoxidil topical solution 2%
■store at20° to 25°C (68° to 77°F). Keep tightyclosed.

Inactive ingredients

aqua, biotin, ollagen, panax ginseng extract ginger extract, safflower extract, cortex dictamni extract, ligusticum chuanxiong
extract, licorioe extract, burdock root extract, angelica sinensis root extract, platycladus orientalis leaf extract, polygonum

muliflorum root extract, aloohol, capsaicin